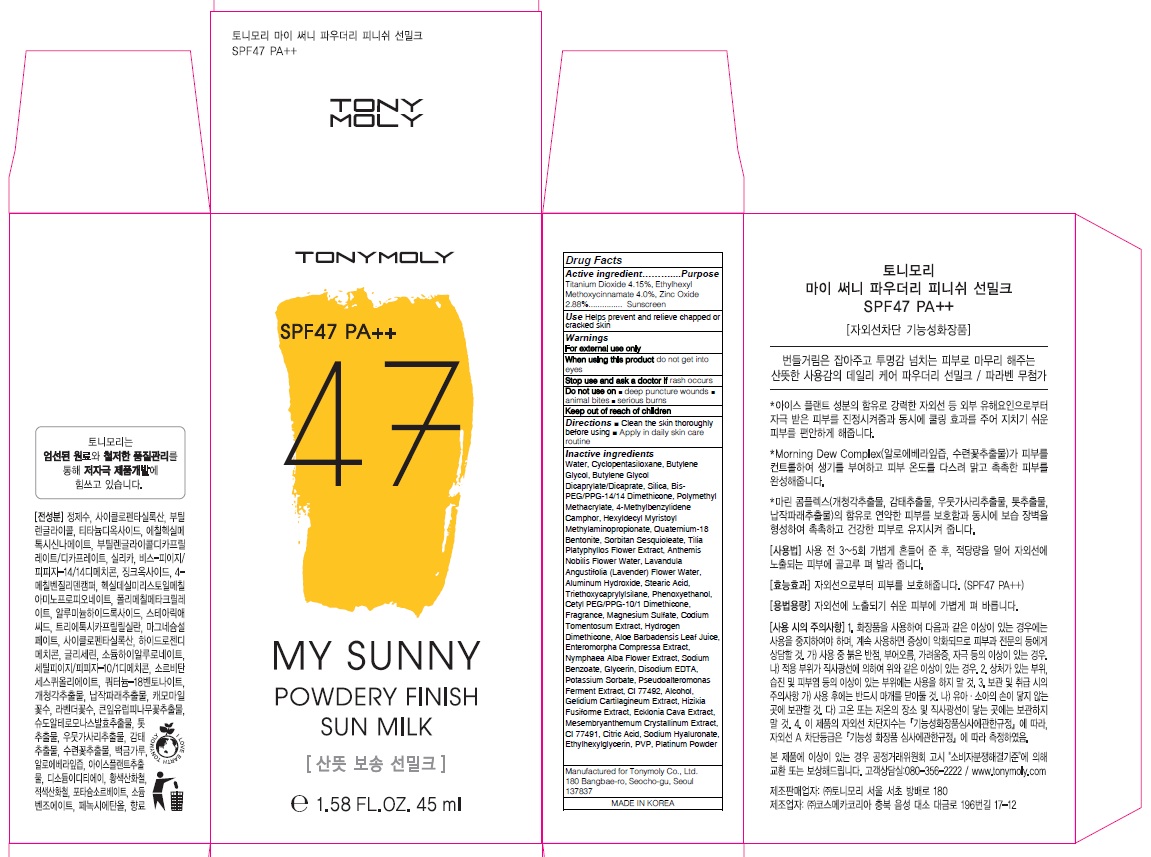 DRUG LABEL: MY SUNNY POWDE RY FINISH SUN MILK
NDC: 59078-309 | Form: CREAM
Manufacturer: TONYMOLY CO.,LTD
Category: otc | Type: HUMAN OTC DRUG LABEL
Date: 20160614

ACTIVE INGREDIENTS: Titanium Dioxide 1.86 g/45 mL; Octinoxate 1.80 g/45 mL; Zinc Oxide 1.29 g/45 mL
INACTIVE INGREDIENTS: Water; Butylene Glycol

ACTIVE INGREDIENT

Active ingredient: Titanium Dioxide 4.15%, Ethylhexyl Methoxycinnamate 4.0%, Zinc Oxide 2.88%

INACTIVE INGREDIENT

Inactive Ingredient: Water, Cyclopentasiloxane, Butylene Glycol, Butylene Glycol Dicaprylate/Dicaprate, Silica, Bis-PEG/PPG-14/14 Dimethicone, Polymethyl Methacrylate, 4-Methylbenzylidene Camphor, Hexyldecyl Myristoyl Methylaminopropionate, Quaternium-18 Bentonite, Sorbitan Sesquioleate, Tilia Platyphyllos Flower Extract, Anthemis Nobilis Flower Water, Lavandula Angustifolia (Lavender) Flower Water, Aluminum Hydroxide, Stearic Acid, Triethoxycaprylylsilane, Phenoxyethanol, Cetyl PEG/PPG-10/1 Dimethicone, Fragrance, Magnesium Sulfate, Codium Tomentosum Extract, Hydrogen Dimethicone, Aloe Barbadensis Leaf Juice, Enteromorpha Compressa Extract, Nymphaea Alba Flower Extract, Sodium Benzoate, Glycerin, Disodium EDTA, Potassium Sorbate, Pseudoalteromonas Ferment Extract, CI 77492, Alcohol, Gelidium Cartilagineum Extract, Hizikia Fusiforme Extract, Ecklonia Cava Extract, Mesembryanthemum Crystallinum Extract, CI 77491, Citric Acid, Sodium Hyaluronate, Ethylhexylglycerin, PVP, Platinum Powder

PURPOSE

Purpose: Sunscreen

WARNINGS

Warnings: For external use only. When using this product do not get into eyes. Stop use and ask a doctor if rash occurs. Do not use on - deep puncture wounds - animal bites - serious burns Keep out of reach of children.

KEEP OUT OF REACH OF CHILDREN

DESCRIPTION

Use: Helps prevent and relieve chapped or cracked skin.

Directions: - Clean the skin thoroughly before using - Apply in daily skin care routine